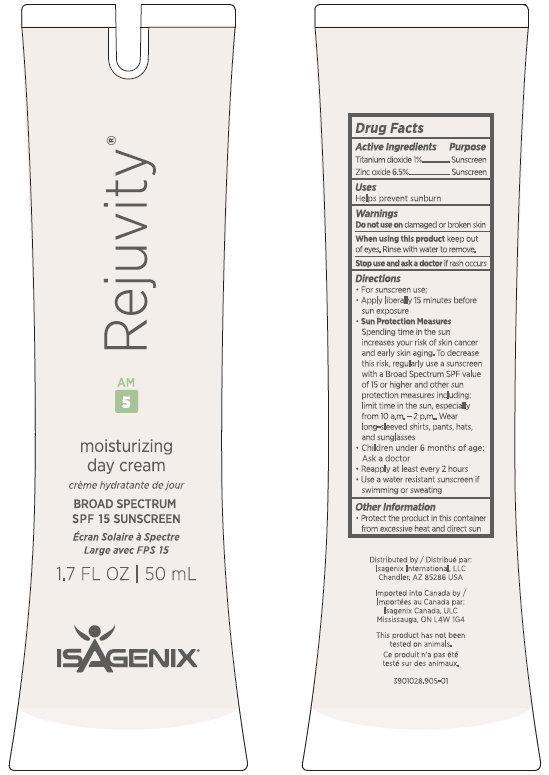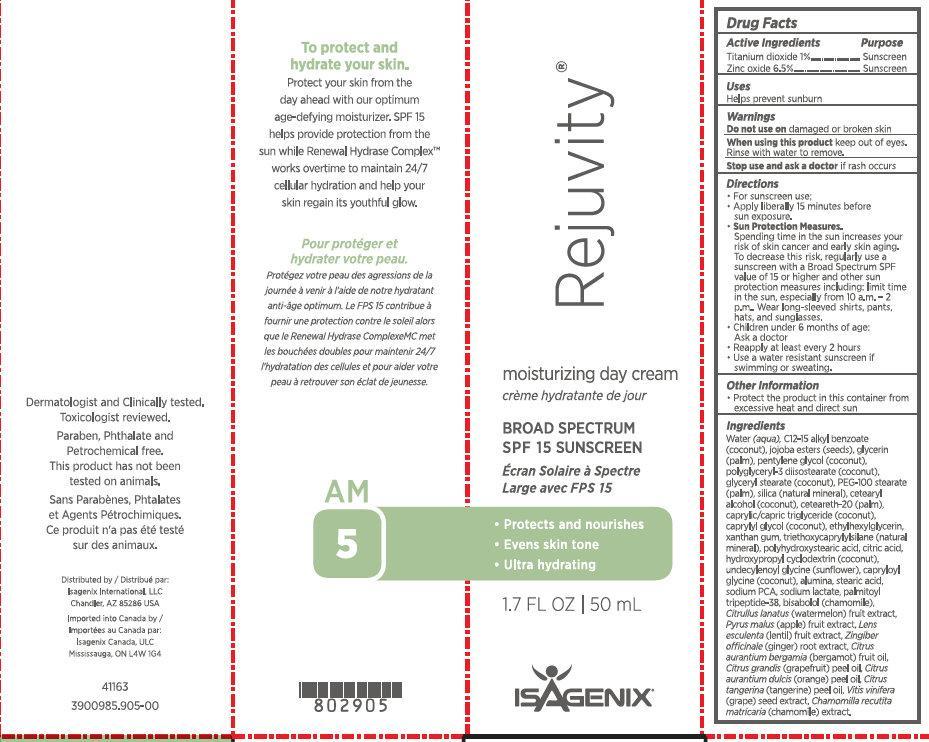 DRUG LABEL: Rejuvity moisturizing day cream BROAD SPECTRUM SPF 15 SUNSCREEN
NDC: 76187-860 | Form: CREAM
Manufacturer: Isagenix International, LLC
Category: otc | Type: HUMAN OTC DRUG LABEL
Date: 20231214

ACTIVE INGREDIENTS: TITANIUM DIOXIDE 10 mg/1 mL; ZINC OXIDE 65 mg/1 mL
INACTIVE INGREDIENTS: WATER; ALKYL (C12-15) BENZOATE; GLYCERIN; PENTYLENE GLYCOL; POLYGLYCERYL-3 DIISOSTEARATE; GLYCERYL MONOSTEARATE; PEG-100 STEARATE; SILICON DIOXIDE; CETOSTEARYL ALCOHOL; POLYOXYL 20 CETOSTEARYL ETHER; MEDIUM-CHAIN TRIGLYCERIDES; CAPRYLYL GLYCOL; ETHYLHEXYLGLYCERIN; XANTHAN GUM; TRIETHOXYCAPRYLYLSILANE; CITRIC ACID MONOHYDRATE; UNDECYLENOYL GLYCINE; CAPRYLOYL GLYCINE; ALUMINUM OXIDE; STEARIC ACID; SODIUM PYRROLIDONE CARBOXYLATE; SODIUM LACTATE; PALMITOYL LYSYLDIOXYMETHIONYLLYSINE; LEVOMENOL; WATERMELON; APPLE; LENS CULINARIS FRUIT; GINGER; BERGAMOT OIL; CITRUS MAXIMA FRUIT RIND OIL; ORANGE OIL; MANDARIN OIL; VITIS VINIFERA SEED

Rejuvity moisturizing day cream BROAD SPECTRUM SPF 15 SUNSCREEN

Active Ingredients

Titanium dioxide 1%
Zinc oxide 6.5%

Purpose

Sunscreen

Uses

Helps prevent sunburn

Warnings

Do not use on

damaged or broken skin

When using this product

keep out of eyes. Rinse with water to remove.

Stop use and ask a doctor

if rash occurs

Keep Out Of Childrens Reach

Directions

- For sunscreen use;
- Apply liberally 15 minutes before sun exposure.
- Sun Protection Measures.
  Spending time in the sun increases your risk of skin cancer and early skin aging. To decrease this risk, regularly use a sunscreen with a Broad Spectrum SPF value of 15 or higher and other sun protection measures including: limit time in the sun, especially from 10 a.m. - 2 p.m.. Wear long-sleeved shirts, pants, hats, and sunglasses.
- Children under 6 months of age: Ask a doctor
- Reapply at least every 2 hours
- Use a water resistant sunscreen if swimming or sweating.

Other Information

- Protect the product in this container from excessive heat and direct sun

Ingredients

Water (aqua), C12-15 alkyl benzoate (coconut), jojoba esters (seeds), glycerin (palm), pentylene glycol (coconut), polyglyceryl-3 diisostearate (coconut), glyceryl stearate (coconut), PEG-100 stearate (palm), silica (natural mineral), cetearyl alcohol (coconut), ceteareth-20 (palm), caprylic/capric triglyceride (coconut), caprylyl glycol (coconut), ethylhexylglycerin, xanthan gum, triethoxycaprylylsilane (natural mineral),
polyhydroxystearic acid, citric acid, hydroxypropyl cyclodextrin (coconut), undecylenoyl glycine (sunflower), capryloyl glycine (coconut), alumina, stearic acid, sodium PCA, sodium lactate, palmitoyl tripeptide-38, bisabolol (chamomile), Citrullus lanatus (watermelon) fruit extract, Pyrus malus (apple) fruit extract, Lens esculenta (lentil) fruit extract, Zingiber officinale (ginger) root extract, Citrus aurantium bergamia (bergamot) fruit oil, Citrus grandis (grapefruit) peel oil, Citrus aurantium dulcis (orange) peel oil, Citrus tangerina (tangerine) peel oil, Vitis vinifera (grape) seed extract, Chamomilla recutita matricaria (chamomile) extract.

moisturizing day cream

To protect and hydrate your skin.
Protect your skin from the day ahead with our optimum age-defying moisturizer. SPF 15 helps provide protection from the sun while Renewal Hydrase Complex works overtime to maintain 24/7 cellular hydration and help your skin regain its youthful glow.

Dermatologist and Clinically tested. Toxicologist reviewed. Paraben, Phthalate and Petrochemical free. This product has not been tested on animals.
Distributed by:
Isagenix International, LLC
Chandler, AZ 85286 USA
Imported into Canada by:
Isagenix Canada, ULC
Mississauga, ON L4W 1G4